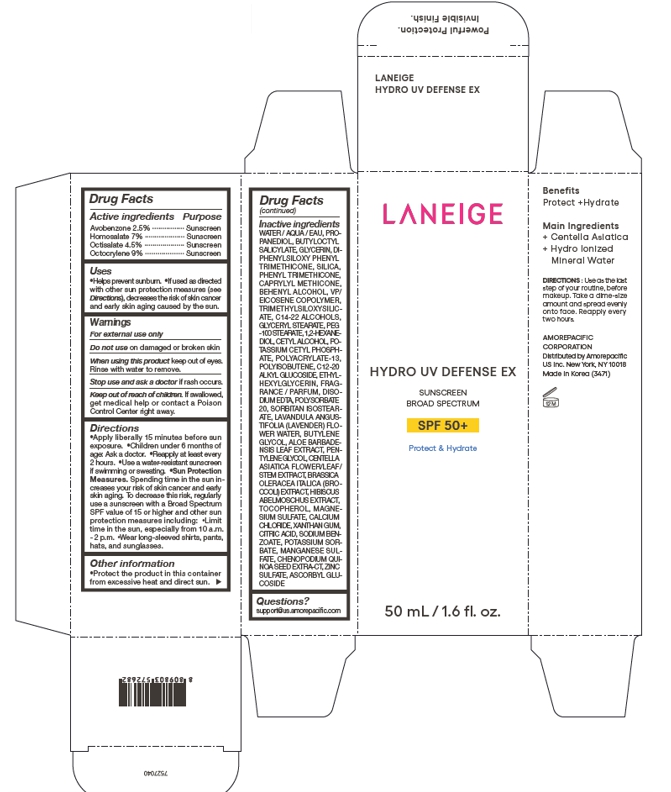 DRUG LABEL: LANEIGE HYDRO UV DEFENSE EX BROAD SPECTRUM SPF 50
NDC: 43419-791 | Form: CREAM
Manufacturer: AMOREPACIFIC CORPORATION
Category: otc | Type: HUMAN OTC DRUG LABEL
Date: 20241008

ACTIVE INGREDIENTS: HOMOSALATE 3.5 g/50 mL; AVOBENZONE 1.25 g/50 mL; OCTOCRYLENE 4.5 g/50 mL; OCTISALATE 2.25 g/50 mL
INACTIVE INGREDIENTS: CHENOPODIUM QUINOA SEED; ABELMOSCHUS MOSCHATUS FLOWER; CALCIUM CHLORIDE; ANHYDROUS CITRIC ACID; POTASSIUM SORBATE; DOCOSANOL; POTASSIUM CETYL PHOSPHATE; BUTYLENE GLYCOL; CENTELLA ASIATICA FLOWERING TOP; .ALPHA.-TOCOPHEROL, DL-; MAGNESIUM SULFATE ANHYDROUS; XANTHAN GUM; SODIUM BENZOATE; ZINC SULFATE MONOHYDRATE; ASCORBYL GLUCOSIDE; POLYSORBATE 20; C14-22 ALCOHOLS; GLYCERYL MONOSTEARATE; PEG-100 STEARATE; C12-20 ALKYL GLUCOSIDE; ETHYLHEXYLGLYCERIN; SORBITAN ISOSTEARATE; CAPRYLYL TRISILOXANE; MANGANESE SULFATE; CETYL ALCOHOL; POLYACRYLATE-13; 1,2-HEXANEDIOL; WATER; PROPANEDIOL; BUTYLOCTYL SALICYLATE; GLYCERIN; SILICON DIOXIDE; VINYLPYRROLIDONE/EICOSENE COPOLYMER; LAVENDER OIL; PHENYL TRIMETHICONE; TRIMETHYLSILOXYSILICATE (M/Q 0.6-0.8); EDETATE DISODIUM ANHYDROUS; ALOE VERA LEAF; PENTYLENE GLYCOL; POLYISOBUTYLENE (1000 MW); DIPHENYLSILOXY PHENYL TRIMETHICONE

LANEIGE HYDRO UV DEFENSE EX BROAD SPECTRUM SPF 50

Active ingredients

Avobenzone 2.5%

Homosalate 7%

Octisalate 4.5%

Octocrylene 9%

Purpose

Sunscreen

Uses

Helps prevent sunburn.

If used as directed with other sun protection measures (see Directions), decreases the risk of skin cancer and early skin aging caused by the sun.

Warnings

For external use only

Do not use on damaged or broken skin

When using this product keep out of eyes. Rinse with water to remove.

Stop use and ask a doctor if rash occurs.

Keep out of reach of children. If swallowed, get medical help or contact a Poison Control Center right away.

Directions

Apply liberally 15 minutes before sun exposure.

Children under 6 months of age: Ask a doctor.

Reapply at least every 2 hours.

Use a water-resistant sunscreen if swimming or sweating.

Sun Protection Measures. Spending time in the sun increases your rick of skin cancer and early skin aging. To decrease this risk, regularly use a sunscreen with a Broad Spectrum SPF value of 15 or higher and other sun protection measures including: Limit time in the sun, especially from 10 a.m.-2 p.m. Wear long-sleeved shirts, pants, hats, and sunglasses.

Other information

Protect the product in this container from excessive heat and direct sun.

Inactive ingredients

WATER, PROPANEDIOL, BUTYLOCTYL SALICYLATE, GLYCERIN, DIPHENYLSILOXY PHENYL TRIMETHICONE, SILICA, PHENYL TRIMETHICONE, CAPRYLYL METHICONE, BEHENYL ALCOHOL, VP/EICOSENE COPOLYMER, TRIMETHYLSILOXYSILICATE, C14-22 ALCOHOLS, GLYCERYL STEARATE, PEG-100 STEARATE, 1,2-HEXANEDIOL, CETYL ALCOHOL, POTASSIUM CETYL PHOSPHATE, POLYACRYLATE-13, POLYISOBUTENE, C12-20 ALKYL GLUCOSIDE, ETHYLHEXYLGLYCERIN, FRAGRANCE / PARFUM, DISODIUM EDTA, POLYSORBATE 20, SORBITAN ISOSTEARATE, LAVANDULA ANGUSTIFOLIA (LAVENDER) FLOWER WATER, BUTYLENE GLYCOL, ALOE BARBADENSIS LEAF EXTRACT, PENTYLENE GLYCOL, CENTELLA ASIATICA FLOWER/LEAF/STEM EXTRACT, BRASSICA OLERACEA ITALICA (BROCCOLI) EXTRACT, HIBISCUS ABELMOSCHUS EXTRACT, TOCOPHEROL, MAGNESIUM SULFATE, CALCIUM CHLORIDE, XANTHAN GUM, CITRIC ACID, SODIUM BENZOATE, POTASSIUM SORBATE, MANGANESE SULFATE, CHENOPODIUM QUINOA SEED EXTRACT, ZINC SULFATE, ASCORBYL GLUCOSIDE

Questions?

support@us.amorepacific.com

LANEIGE HYDRO UV DEFENSE EX

LANEIGE

HYDRO UV DEFENSE EX

SUNSCREEN

BROAD SPECTRUM SPF 50+

50 mL / 1.6 fl. oz.